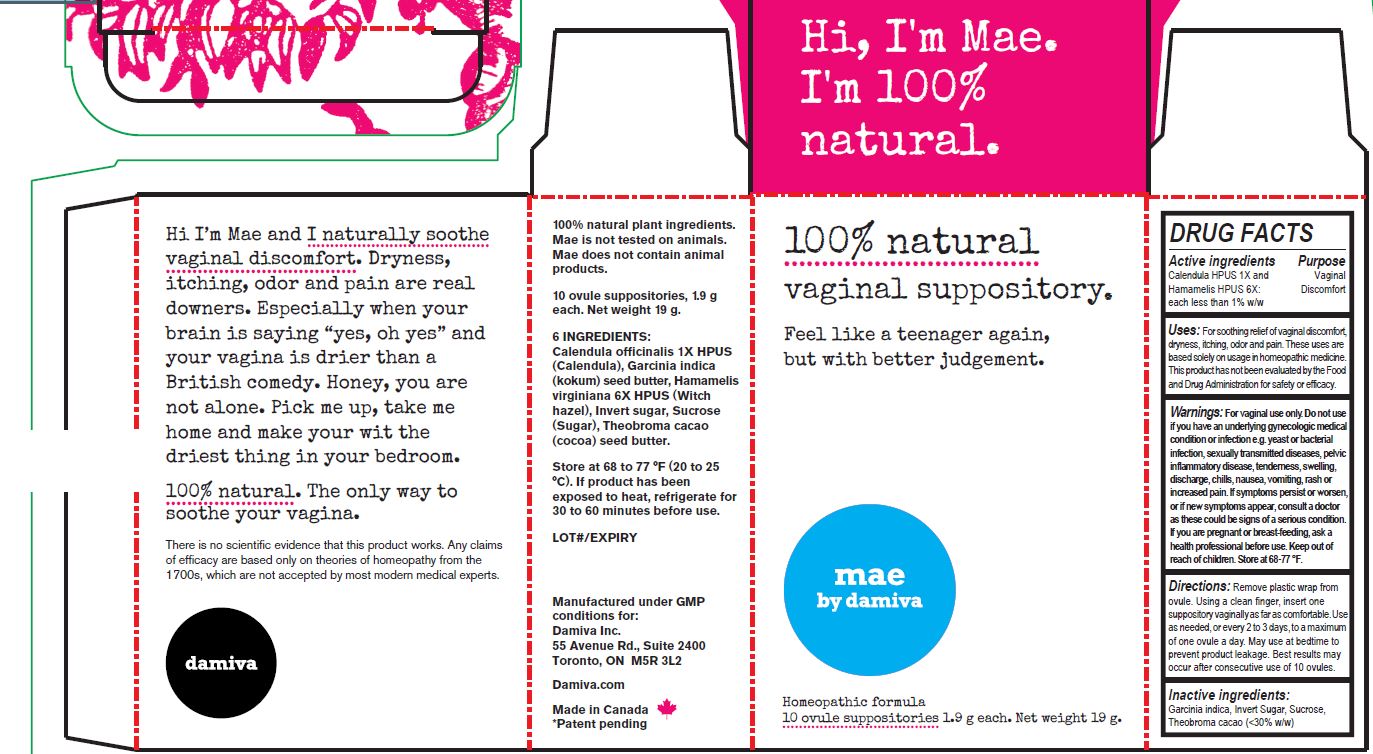 DRUG LABEL: Mae by Damiva
NDC: 69316-321 | Form: SUPPOSITORY
Manufacturer: Damiva Inc.
Category: homeopathic | Type: HUMAN OTC DRUG LABEL
Date: 20181231

ACTIVE INGREDIENTS: CALENDULA OFFICINALIS FLOWER 1 [hp_X]/1 1; HAMAMELIS VIRGINIANA LEAF 6 [hp_X]/1 1
INACTIVE INGREDIENTS: GARCINIA INDICA SEED BUTTER; SUCROSE; COCOA BUTTER

Mae by Damiva

DRUG FACTS

Active ingredients

Calendula HPUS 1X and

Hamamelis HPUS 6X:

each less than 1% w/w

Purpose

Vaginal Discomfort

INDICATIONS AND USAGE

Uses: For soothing relief of vaginal discomfort, dryness, itching, odor and pain. These uses are based solely on usage in homeopathic medicine. This product has not been evaluated by the Food and Drug Administration for safety or efficacy.

Warnings

For vaginal use only.

Do not use if you have an underlying gynecological medical condition or infection e.g. yeast or bacterial infection, sexually transmitted diseases, pelvic inflammatory disease, tenderness, swelling, discharge, chills, nausea, vomiting, rash or increased pain.

ASK DOCTOR

If symptoms persist or worsen, or if new symptoms appear, consult a doctor as these could be signs of a serious condition.

PREGNANCY OR BREAST FEEDING

If you are pregnant or breast-feeding, ask a health professional before use.

Keep out of reach of children.

OTHER SAFETY INFORMATION

Store at 68-77 °F.

DOSAGE AND ADMINISTRATION

Directions: Remove plastic wrap from ovule. Using a clean finger, insert one suppository vaginally as far as comfortable. Use as needed, or every 2 to 3 days, to a maximum of one ovule per day. May use at bedtime to prevent product leakage. Best results may occur after consecutive use of 10 ovules.

Inactive ingredients:

Garcinia indica, Invert Sugar, Sucrose, Theobroma cacao (<30% w/w)

PACKAGE LABEL

100% natural
vaginal suppository.

Feel like a teenager again,
but with better judgement.

mae
by damiva

Homeopathic formula
10 ovule suppositories 1.9 g each. Net weight 19 g.